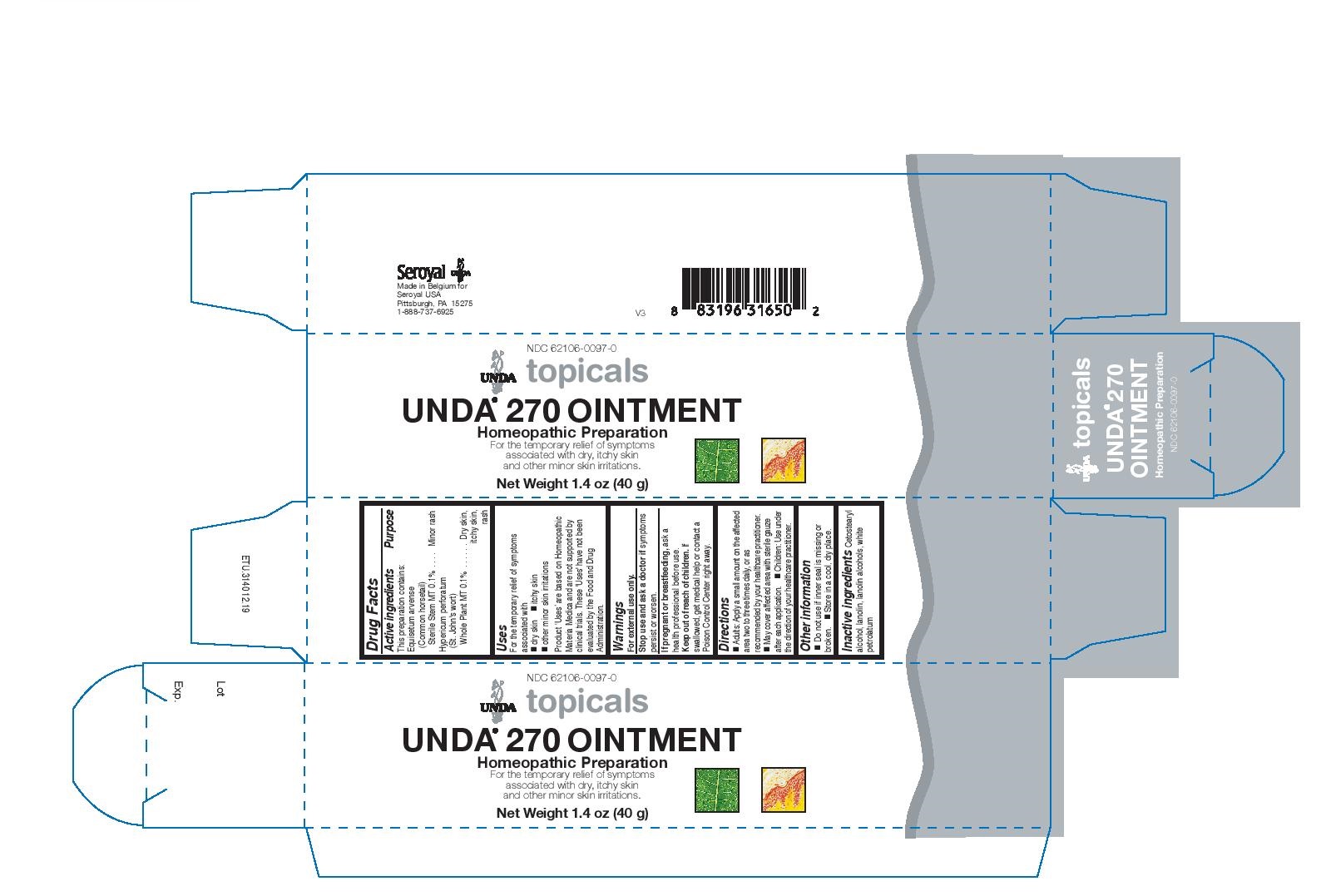 DRUG LABEL: UNDA 270
NDC: 62106-0097 | Form: CREAM
Manufacturer: Seroyal USA
Category: homeopathic | Type: HUMAN OTC DRUG LABEL
Date: 20200923

ACTIVE INGREDIENTS: HYPERICUM PERFORATUM 1 [hp_X]/40 g; EQUISETUM ARVENSE TOP 1 [hp_X]/40 g
INACTIVE INGREDIENTS: PETROLATUM; CETOSTEARYL ALCOHOL; LANOLIN

UNDA 270 OINTMENT

Active ingredients
This preparation contains:
Equisetum arvense (Common horsetail) Sterile Stem MT 0.1%
Hypericum perforatum (St. John's wort) Whole Plant MT 0.1%

Uses
For the temporary relief of symptoms associated with

dry skin

itchy skin
other minor skin irritations

Warnings
For external use only.
Stop use and ask a doctor if symptoms persist or worsen.
If pregnant or breastfeeding, ask a health professional before use.
Keep out of reach of children. If swallowed, get medical help or contact a
Poison Control Center right away.

Keep out of reach of children.

OVERDOSAGE

If swallowed, get medical help or contact a Poison Control Center right away.

Inactive ingredients

Cetostearyl alcohol, lanolin, lanolin alcohols, white petrolatum

Other information
Do not use if inner seal is missing or broken.

Store in a cool, dry place

Directions
Adults: Apply a small amount on the affected area two to three times daily, or as recommended by your healthcare practitioner.

May cover affected area with sterile gauze after each application.

Children: Use under the direction of your healthcare practitioner.

Uses
For the temporary relief of symptoms associated with

dry skin

itchy skin
other minor skin irritations

Directions
Adults: Apply a small amount on the affected area two to three times daily, or as recommended by your healthcare practitioner.

May cover affected area with sterile gauze after each application.

Children: Use under the direction of your healthcare practitioner.

PACKAGE LABEL

NDC 62106-0097-0

UNDA topicals

UNDA 270 OINTMENT

Homeopathic Preparation

For the temporary relief of symptoms
associated with dry, itchy skin
and other minor skin irritations.

Net Weight 1.4 oz (40 g)